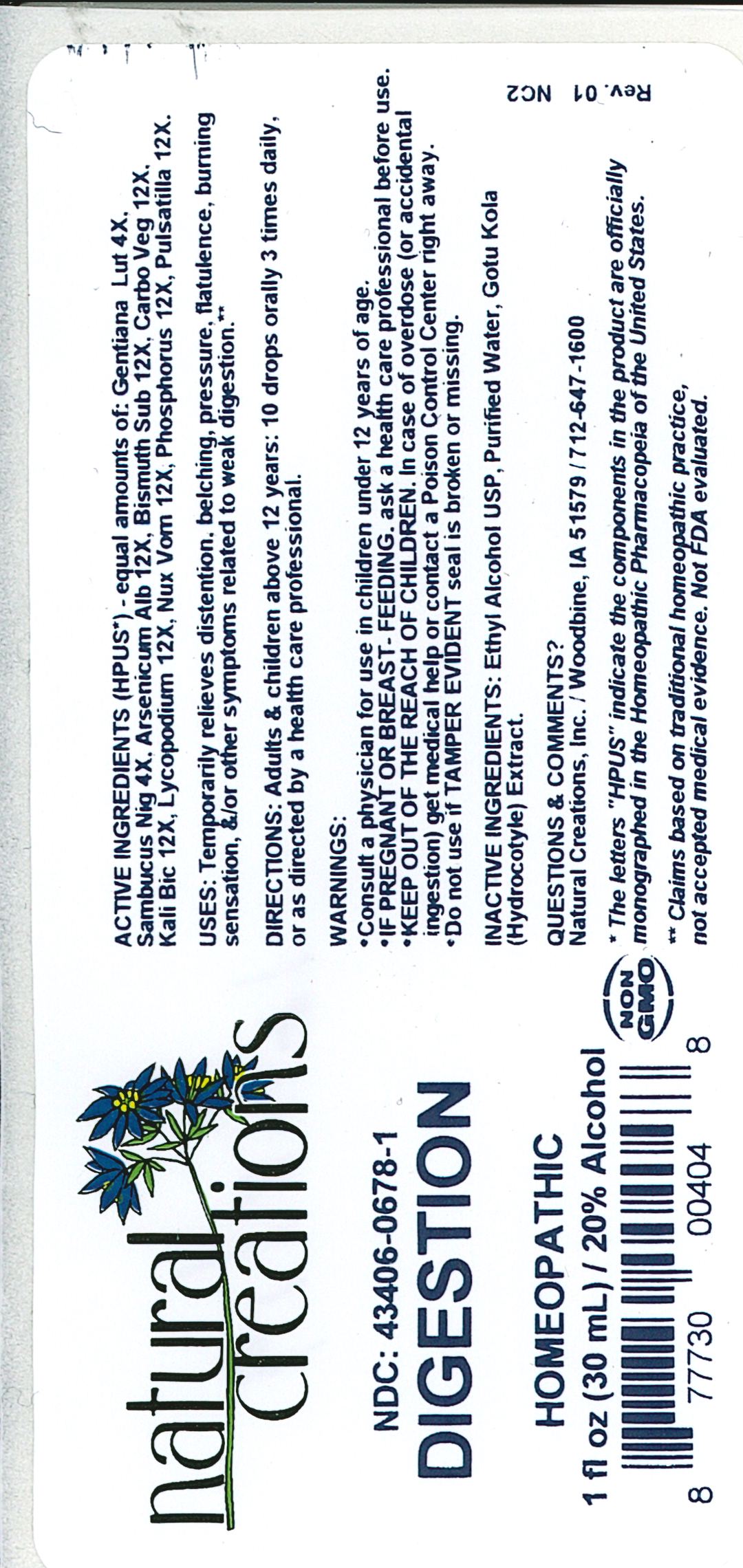 DRUG LABEL: Digestion
NDC: 43406-0678 | Form: LIQUID
Manufacturer: Natural Creations, Inc
Category: homeopathic | Type: HUMAN OTC DRUG LABEL
Date: 20251210

ACTIVE INGREDIENTS: GENTIANA LUTEA ROOT 4 [hp_X]/1 mL; SAMBUCUS NIGRA FLOWERING TOP 4 [hp_X]/1 mL; ARSENIC TRIOXIDE 12 [hp_X]/1 mL; BISMUTH SUBNITRATE 12 [hp_X]/1 mL; ACTIVATED CHARCOAL 12 [hp_X]/1 mL; POTASSIUM DICHROMATE 12 [hp_X]/1 mL; LYCOPODIUM CLAVATUM SPORE 12 [hp_X]/1 mL; STRYCHNOS NUX-VOMICA SEED 12 [hp_X]/1 mL; PHOSPHORUS 12 [hp_X]/1 mL; PULSATILLA VULGARIS WHOLE 12 [hp_X]/1 mL
INACTIVE INGREDIENTS: ALCOHOL; WATER; CENTELLA ASIATICA LEAF

Digestion

ACTIVE INGREDIENT

ACTIVE INGREDIENTS (HPUS*) - equal amounts of: Gentiana Lut 4X, Sambucus Nig 4X, Arsenicum Alb 12X, Bismuth Sub 12X, Carbo Veg 12X, Kali Bic 12X, Lycopodium 12X, Nux Vom 12X, Phosphorus 12X, Pulsatilla 12X.

INDICATIONS AND USAGE

USES: Temporarily relieves distention, belching, pressure, flatulence, burning sensation, &/or other symptoms related to weak digestion.**

PURPOSE

USES: Temporarily relieves distention, belching, pressure, flatulence, burning sensation, &/or other symptoms related to weak digestion.**

DOSAGE AND ADMINISTRATION

DIRECTIONS: Adults & children above 12 years: 10 drops orally 3 times daily, or as directed by a health care professional.

KEEP OUT OF REACH OF CHILDREN

KEEP OUT OF THE REACH OF CHILDREN. In case of overdose (or accidental ingestion) get medical help or contact a Poison Control Center right away.

WARNINGS:

- Consult a physician for use in children under 12 years of age.
- IF PREGNANT OR BREAST-FEEDING, ask a health care professional before use.
- KEEP OUT OF THE REACH OF CHILDREN. In case of overdose (or accidental ingestion) get medical help or contact a Poison Control Center right away.
- Do not use if TAMPER EVIDENT seal is broken or missing.

INACTIVE INGREDIENT

INACTIVE INGREDIENTS: Ethyl Alcohol USP, Purified Water, Gotu Kola (Hydrocotyle) Extract.

QUESTIONS & COMMENTS?

Natural Creations, Inc. / Woodbine, IA 51579 / 712-647-1600

REFERENCES

* The letters "HPUS" indicate the components in the product are officially monographed in the Homeopathic Pharmacopeia of the United States.

**Claims based on traditional homeopathic practice, not accepted medical evidence. Not FDA evaluated.

PACKAGE LABEL

NDC: 43406-0678-1

DIGESTION

HOMEOPATHIC

1 fl oz (30mL) / 20% Alcohol